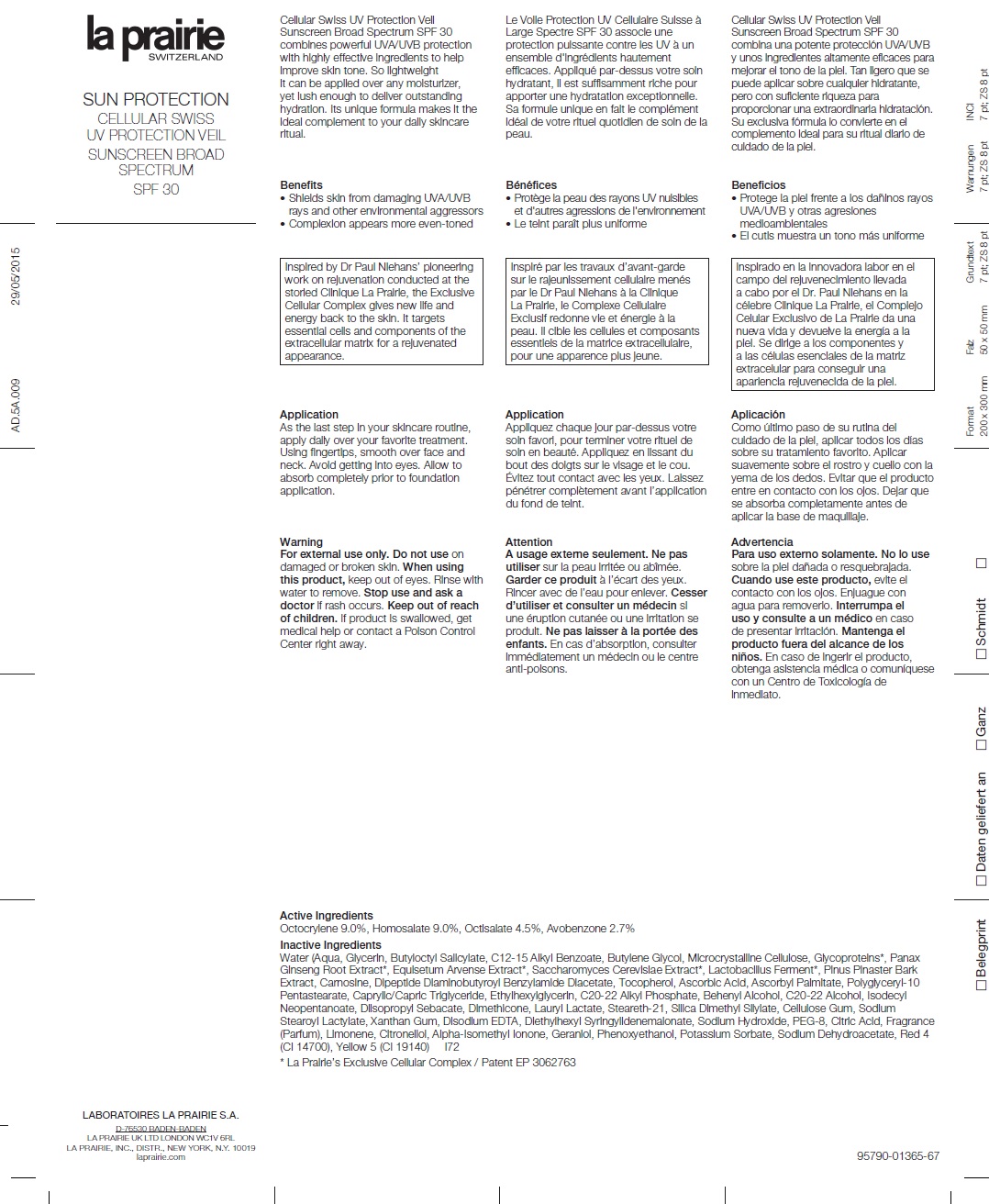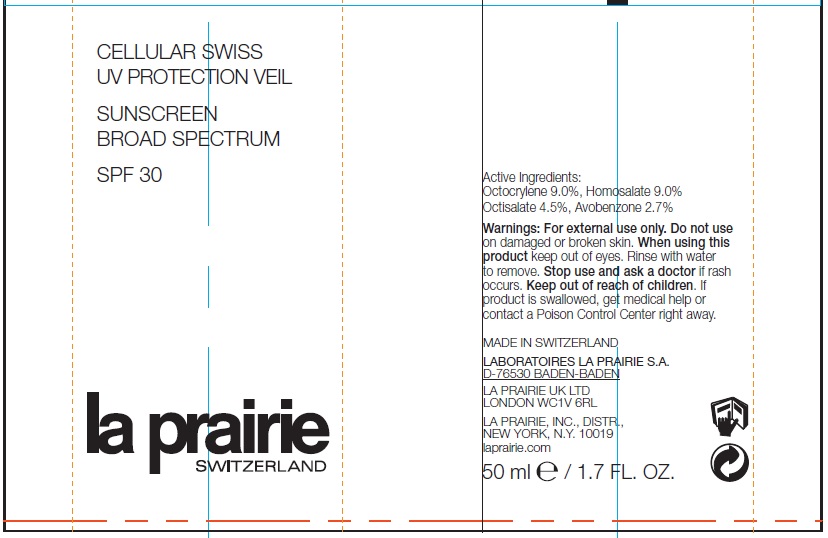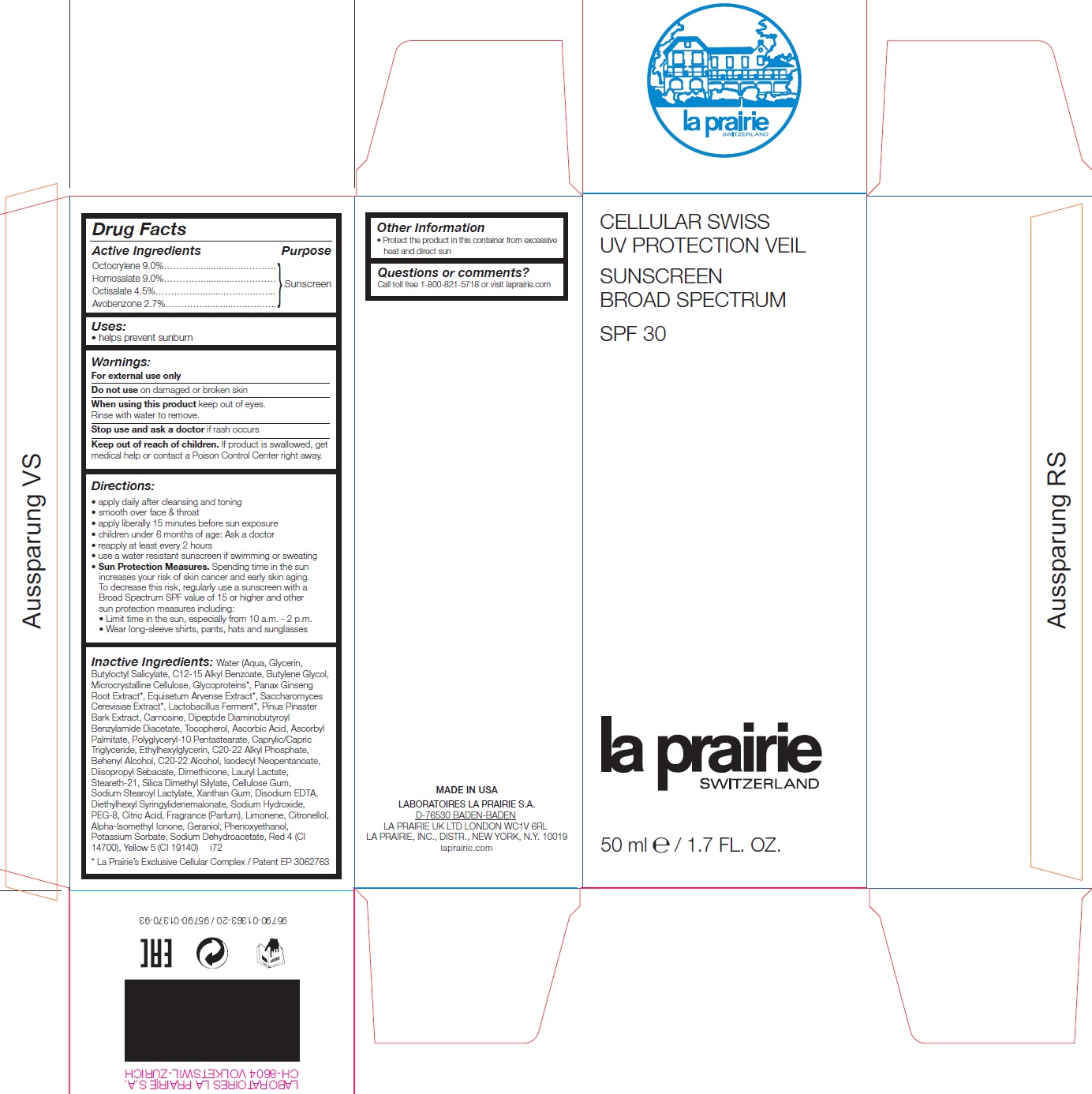 DRUG LABEL: Cellular Swiss UV Protection Veil SPF30
NDC: 68026-809 | Form: CREAM
Manufacturer: La Prairie, Inc.
Category: otc | Type: HUMAN OTC DRUG LABEL
Date: 20250221

ACTIVE INGREDIENTS: OCTOCRYLENE 90 mg/1 mL; HOMOSALATE 90 mg/1 mL; OCTISALATE 45 mg/1 mL; AVOBENZONE 27 mg/1 mL
INACTIVE INGREDIENTS: WATER; GLYCERIN; BUTYLOCTYL SALICYLATE; ALKYL (C12-15) BENZOATE; BUTYLENE GLYCOL; MICROCRYSTALLINE CELLULOSE; ASIAN GINSENG; EQUISETUM ARVENSE BRANCH; SACCHAROMYCES CEREVISIAE; MARITIME PINE; CARNOSINE; DIPEPTIDE DIAMINOBUTYROYL BENZYLAMIDE DIACETATE; TOCOPHEROL; ASCORBIC ACID; ASCORBYL PALMITATE; POLYGLYCERYL-10 PENTASTEARATE; MEDIUM-CHAIN TRIGLYCERIDES; ETHYLHEXYLGLYCERIN; C20-22 ALKYL PHOSPHATE; DOCOSANOL; C20-22 ALCOHOLS; ISODECYL NEOPENTANOATE; DIISOPROPYL SEBACATE; DIMETHICONE; LAURYL LACTATE; STEARETH-21; SILICA DIMETHYL SILYLATE; CARBOXYMETHYLCELLULOSE SODIUM, UNSPECIFIED; SODIUM STEAROYL LACTYLATE; XANTHAN GUM; EDETATE DISODIUM ANHYDROUS; DIETHYLHEXYL SYRINGYLIDENEMALONATE; SODIUM HYDROXIDE; POLYETHYLENE GLYCOL 400; CITRIC ACID MONOHYDRATE; LIMONENE, (+)-; .BETA.-CITRONELLOL, (R)-; ISOMETHYL-.ALPHA.-IONONE; GERANIOL; PHENOXYETHANOL; POTASSIUM SORBATE; SODIUM DEHYDROACETATE; FD&C RED NO. 4; FD&C YELLOW NO. 5

Cellular Swiss UV Protection Veil SPF30

Active Ingredients

Octocrylene 9.0%

Homosalate 9.0%

Octisalate 4.5%

Avobenzone 2.7%

Purpose

Sunscreen

Uses:

• helps prevent sunburn

Warnings:

For external use only

Do not use

on damaged or broken skin

When using this product

keep out of eyes. Rinse with water to remove.

Stop use and ask a doctor

if rash occurs

Keep out of reach of children.

If product is swallowed, get medical help or contact a Poison Control Center right away.

Directions:

• apply daily after cleansing and toning
• smooth over face & throat
• apply liberally 15 minutes before sun exposure
• children under 6 months of age: Ask a doctor
• reapply at least every 2 hours
• use a water resistant sunscreen if swimming or sweating
• Sun Protection Measures. Spending time in the sun increases your risk of skin cancer and early skin aging. To decrease this risk, regularly use a sunscreen with a Broad Spectrum SPF value of 15 or higher and other sun protection measures including:
• Limit time in the sun, especially from 10 a.m. - 2 p.m.
• Wear long-sleeve shirts, pants, hats and sunglasses

Inactive Ingredients:

Water (Aqua, Glycerin, Butyloctyl Salicylate, C12-15 Alkyl Benzoate, Butylene Glycol, Microcrystalline Cellulose, Glycoproteins*, Panax Ginseng Root Extract*, Equisetum Arvense Extract*, Saccharomyces Cerevisiae Extract*, Lactobacillus Ferment*, Pinus Pinaster Bark Extract, Carnosine, Dipeptide Diaminobutyroyl Benzylamide Diacetate, Tocopherol, Ascorbic Acid, Ascorbyl Palmitate, Polyglyceryl-10 Pentastearate, Caprylic/Capric Triglyceride, Ethylhexylglycerin, C20-22 Alkyl Phosphate, Behenyl Alcohol, C20-22 Alcohol, Isodecyl Neopentanoate, Diisopropyl Sebacate, Dimethicone, Lauryl Lactate, Steareth-21, Silica Dimethyl Silylate, Cellulose Gum, Sodium Stearoyl Lactylate, Xanthan Gum, Disodium EDTA, Diethylhexyl Syringylidenemalonate, Sodium Hydroxide, PEG-8, Citric Acid, Fragrance (Parfum), Limonene, Citronellol, Alpha-Isomethyl Ionone, Geraniol, Phenoxyethanol, Potassium Sorbate, Sodium Dehydroacetate, Red 4 (CI 14700), Yellow 5 (CI 19140) i72
* La Prairie’s Exclusive Cellular Complex / Patent EP 3062763

Other Information

• Protect the product in this container from excessive heat and direct sun

Questions or comments?

Call toll free 1-800-821-5718 or visit laprairie.com